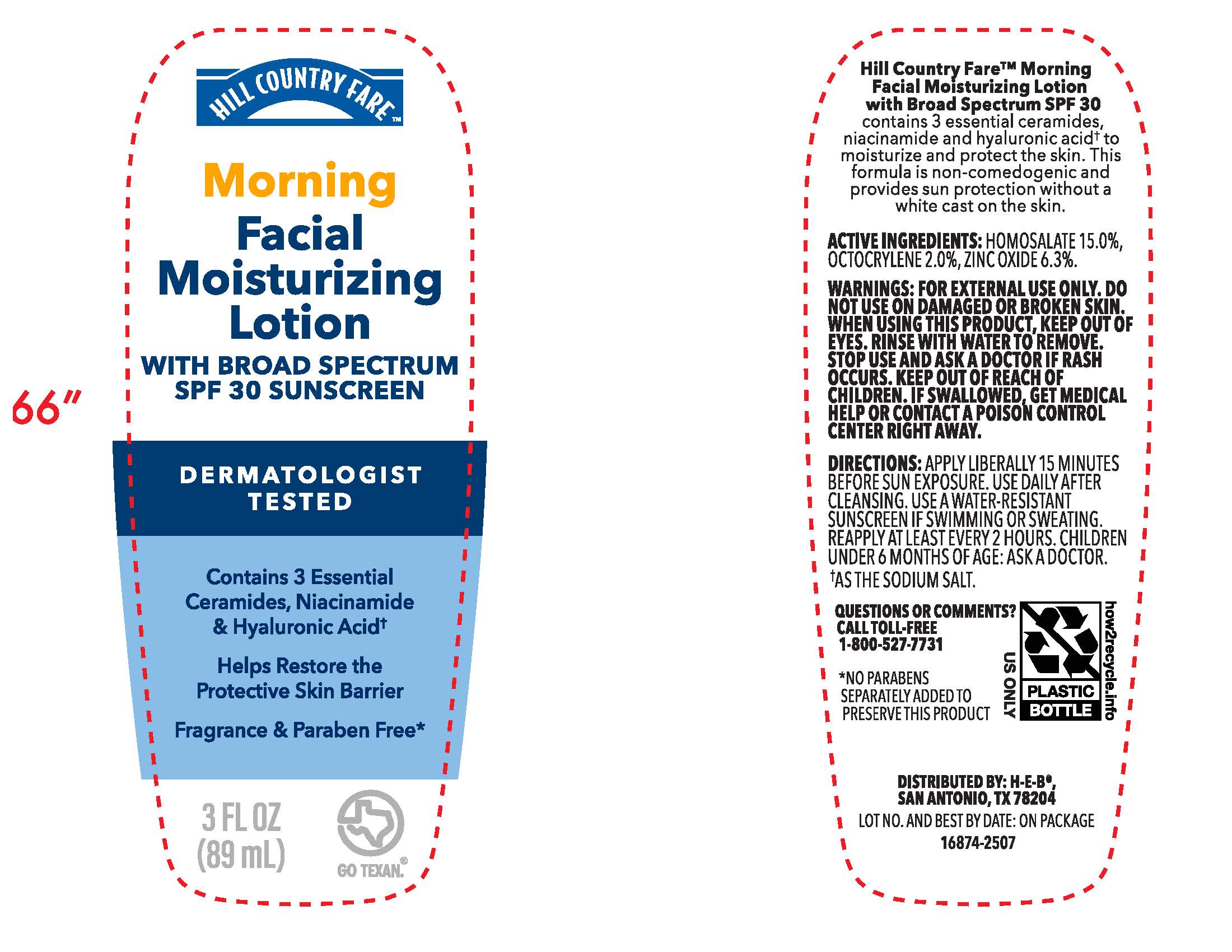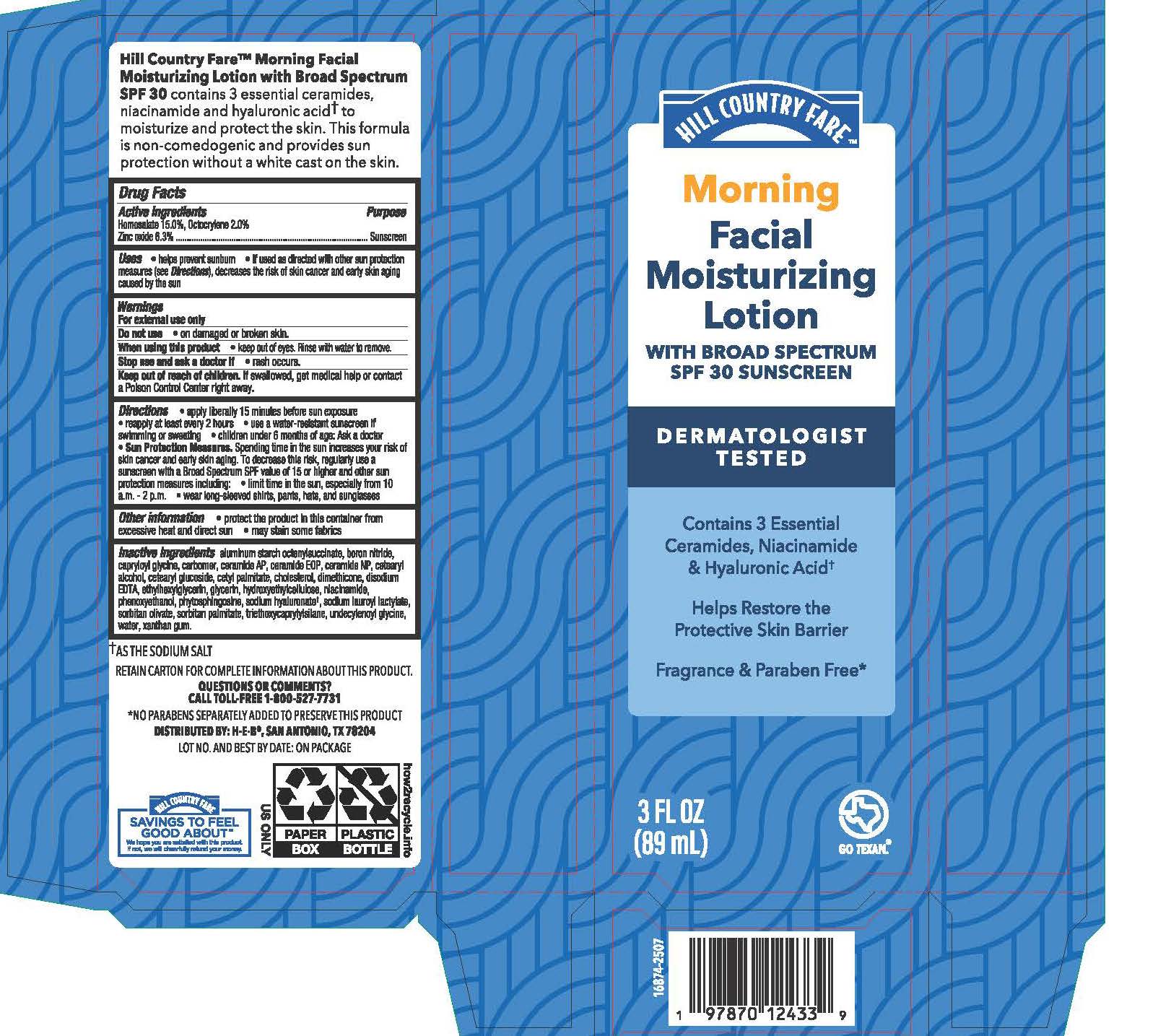 DRUG LABEL: Hill Country Fare Morning Facial Moisturizing with Broad Spectrum SPF 30 Sunscreen
NDC: 37808-939 | Form: LOTION
Manufacturer: H.E.B.
Category: otc | Type: HUMAN OTC DRUG LABEL
Date: 20251118

ACTIVE INGREDIENTS: ZINC OXIDE 6.3 mg/100 mL; HOMOSALATE 15 mg/100 mL; OCTOCRYLENE 2 mg/100 mL
INACTIVE INGREDIENTS: TRIETHOXYCAPRYLYLSILANE; XANTHAN GUM; PHENOXYETHANOL; CERAMIDE AP; CERAMIDE NP; CETYL PALMITATE; SORBITAN OLIVATE; CAPRYLOYL GLYCINE; HYDROXYETHYL CELLULOSE (2000 CPS AT 1%); UNDECYLENOYL GLYCINE; CETEARYL ALCOHOL; SORBITAN PALMITATE; BORON NITRIDE; DIMETHICONE; SODIUM HYALURONATE; CETEARYL GLUCOSIDE; WATER; ALUMINUM STARCH OCTENYLSUCCINATE; NIACINAMIDE; GLYCERIN; CERAMIDE 1; EDETATE DISODIUM; PHYTOSPHINGOSINE; POLYACRYLIC ACID (450000 MW); CHOLESTEROL; ETHYLHEXYLGLYCERIN; SODIUM LAUROYL LACTYLATE

Morning Facial Moisturizing Lotion with Broad Spectrum SPF 30 Sunscreen

Active Ingredients

Homosalate 15.0%, Octocrylene 2.0%, Zinc Oxide 6.3%

Purpose

Sunscreen

Uses

- helps prevent sunburn
- if used as directed with other sun protection measures (see Directions), decreases the risk of skin cancer and early skin aging caused by the sun.

Warnings

For external use only

Do not use

- on damaged or broken skin

When using this product

- keep out of eyes. Rinse with water to remove.

Stop use and ask a doctor if

- rash occurs.

Keep out of reach of children.

If swallowed, get medical help or contact a Poison Control Center right away.

Directions

- apply liberally 15 minutes before sun exposure
- reapply at least every 2 hours
- use a water-resistant sunscreen if swimming or sweating
- children under 6 months of age: Ask a doctor
- Sun Protection Measures. Spending time in the sun increases your risk of skin cancer and early skin aging. To decrease this risk, regularly use a sunscreen with a Broad Spectrum SPF value of 15 or higher and other sun protection measures including: ▪ limit time in the sun, especially from 10 a.m. - 2 p.m. ▪ wear long-sleeved shirts, pants, hats, and sunglasses

Other information

- protect the product in this container from excessive heat and direct sun
- may stain some fabrics

Inactive ingredients

aluminum starch octenylsuccinate, boron nitride, capryloyl glycine, carbomer, ceramide AP, ceramide EOP, ceramide NP, cetearyl alcohol, cetearyl glucoside, cetyl palmitate, cholesterol, dimethicone, disodium EDTA, ethylhexylglycerin, glycerin, hydroxyethylcellulose, niacinamide, phenoxyethanol, phytosphingosine, sodium hyaluronate, sodium lauroyl lactylate, sorbitan olivate, sorbitan palmitate, triethoxycaprylylsilane, undecylenoyl glycine, water, xanthan gum.